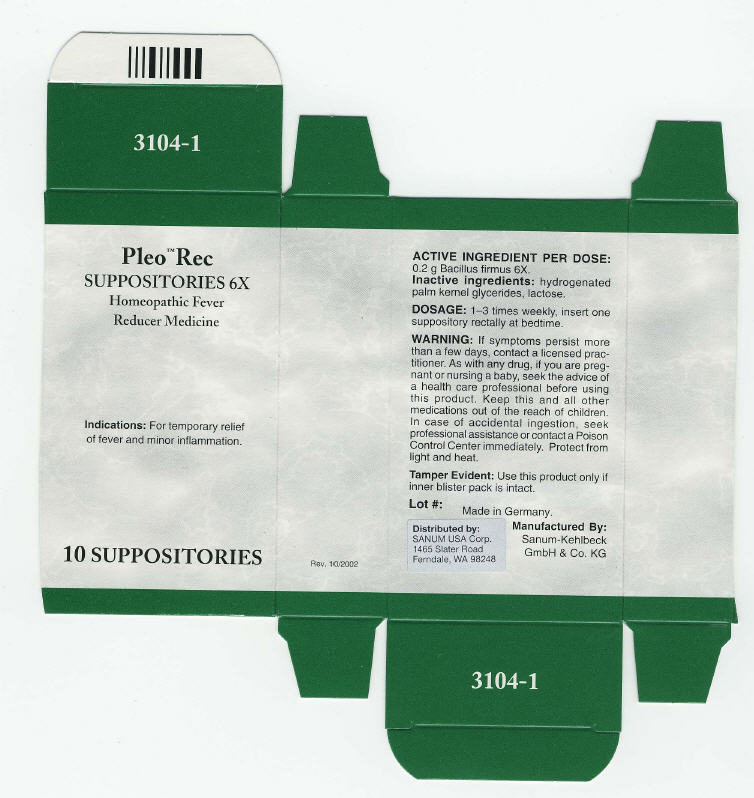 DRUG LABEL: Pleo Rec
NDC: 60681-3104 | Form: SUPPOSITORY
Manufacturer: Sanum Kehlbeck GmbH & Co. KG
Category: homeopathic | Type: HUMAN OTC DRUG LABEL
Date: 20091014

ACTIVE INGREDIENTS: bacillus firmus 6 [HP_X]/1 1
INACTIVE INGREDIENTS: lactose

Pleo™ Rec
SUPPOSITORIES 6X

Homeopathic Fever Reducer Medicine

10 SUPPOSITORIES

Indications

For temporary relief of fever and minor inflammation.

ACTIVE INGREDIENT PER DOSE

0.2 g Bacillus firmus 6X.

Inactive ingredients

hydrogenated palm kernel glycerides, lactose.

DOSAGE

1–3 times weekly, insert one suppository rectally at bedtime.

WARNING

If symptoms persist more than a few days, contact a licensed practitioner. As with any drug, if you are pregnant or nursing a baby, seek the advice of a health care professional before using this product.

KEEP OUT OF REACH OF CHILDREN

Keep this and all other medications out of the reach of children. In case of accidental ingestion, seek professional assistance or contact a Poison Control Center immediately.

STORAGE AND HANDLING

Protect from light and heat.

Tamper Evident

Use this product only if inner blister pack is intact.

Made in Germany.

Distributed by:
SANUM USA Corp.
1465 Slater Road
Ferndale, WA 98248

Manufactured By:
Sanum-Kehlbeck
GmbH & Co. KG

Rev. 10/2002

PRINCIPAL DISPLAY PANEL - 10 Suppository Carton

Pleo™ Rec
SUPPOSITORIES 6X

Homeopathic Fever
Reducer Medicine

Indications: For temporary relief
of fever and minor inflammation.

10 SUPPOSITORIES